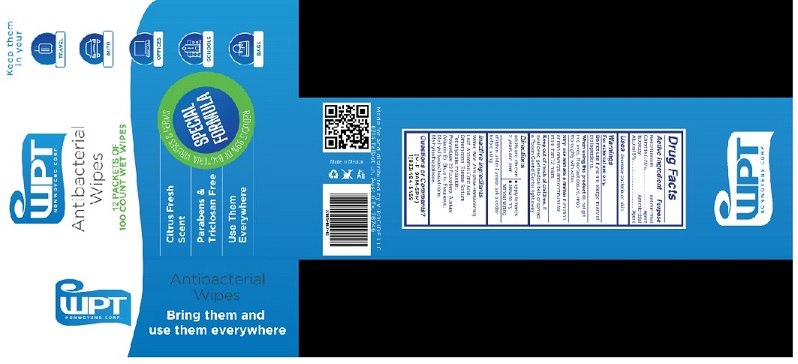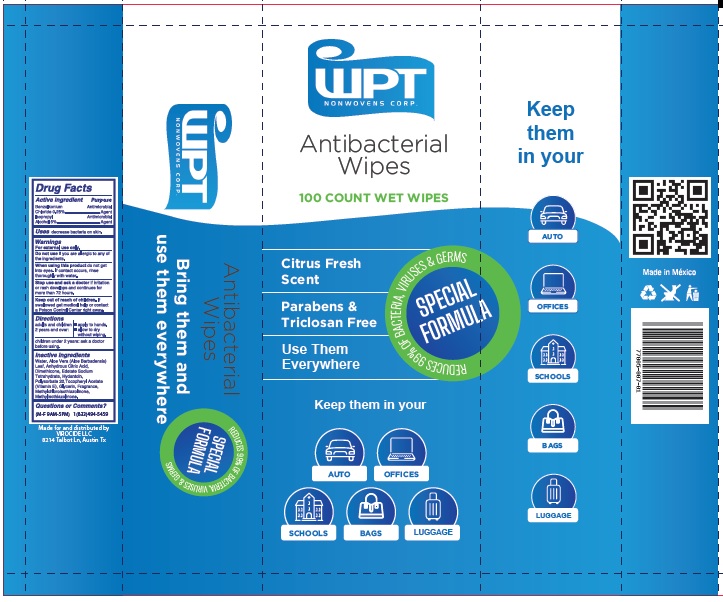 DRUG LABEL: Virocide Antibacterial Wipes
NDC: 77005-007 | Form: CLOTH
Manufacturer: Virocide LLC
Category: otc | Type: HUMAN OTC DRUG LABEL
Date: 20201007

ACTIVE INGREDIENTS: BENZALKONIUM CHLORIDE 2.5 mg/1 1; ISOPROPYL ALCOHOL 5 mL/1 1
INACTIVE INGREDIENTS: WATER; ALOE VERA LEAF; ANHYDROUS CITRIC ACID; DIMETHICONE; EDETATE SODIUM TETRAHYDRATE; HYDANTOIN; POLYSORBATE 20; .ALPHA.-TOCOPHEROL ACETATE; GLYCERIN; METHYLCHLOROISOTHIAZOLINONE; METHYLISOTHIAZOLINONE

Virocide Antibacterial Wipes

Drug Facts

Active ingredient
Benzalkonium Chloride 0.25%
Isopropyl Alcohol 5%

Purpose
Benzalkonium Chloride .......................... Antimicrobial Agent
Isopropyl Alcohol ................................... Antimicrobial Agent

INDICATIONS AND USAGE

Uses decrease bacteria on skin.

Warnings
For external use only.

When using this product, avoid contact with the eyes.
In case of contact, rinse eyes thoroughly with water.

Do not use if you are allergic to any of
the ingredients.

When using this product do not get
into eyes. If contact occurs, rinse
thoroughly with water.

Stop use and ask a doctor if irritation
or rash develops and continues for
more than 72 hours.

Keep out of reach of children. If
swallowed get medical help or contact
a Poison Control Center right away.

Directions
adults and children ■ apply to hands.
2 years and over: ■ allow to dry
without wiping.
children under 2 years: ask a doctor
before using.

Questions or Comments?
(M-F 9AM-5PM)
1(833)494-5459

Inactive Ingredients
Water, Aloe Vera (Aloe Barbadensis)
Leaf, Anhydrous Citric Acid,
Dimethicone, Edetate Sodium
Tetrahydrate, Hydantoin,
Polysorbate 20,Tocopheryl Acetate
(Vitamin E), Glycerin, Fragrance,
Methylchloroisothiazolinone,
Methylisothiazolinone.

Package Label

BOX OF 12-PACKETS

PACKET OF 100 WIPES

res